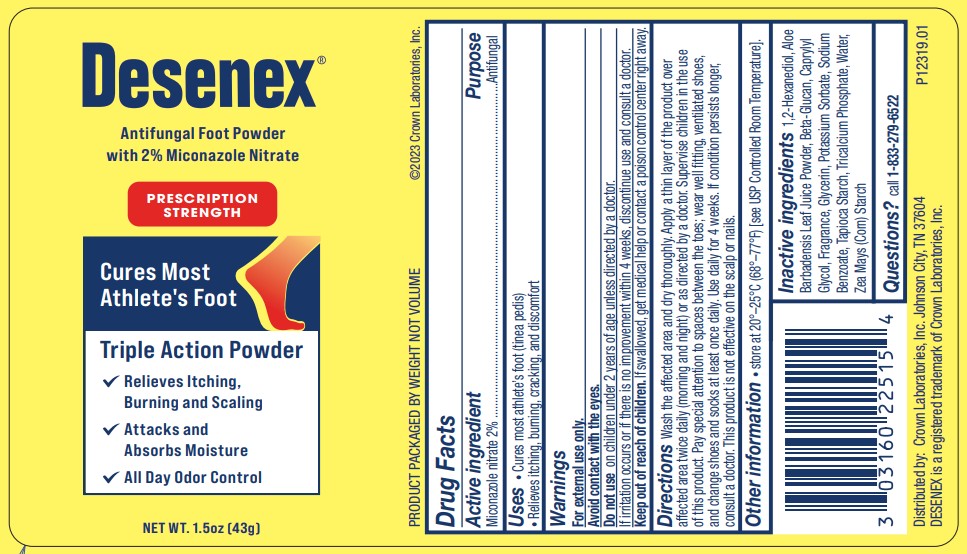 DRUG LABEL: Desenex
NDC: 0316-0225 | Form: POWDER
Manufacturer: Crown Laboratories
Category: otc | Type: HUMAN OTC DRUG LABEL
Date: 20260112

ACTIVE INGREDIENTS: MICONAZOLE NITRATE 20 mg/1 g
INACTIVE INGREDIENTS: STARCH, TAPIOCA; TRICALCIUM PHOSPHATE; CAPRYLYL GLYCOL; WATER; STARCH, CORN; 1,2-HEXANEDIOL; ALOE VERA LEAF; YEAST .BETA.-D-GLUCAN; GLYCERIN; POTASSIUM SORBATE; SODIUM BENZOATE

Desenex

Active ingredient

Miconazole nitrate 2%

Purpose

Antifungal

Uses

- Cures most athlete’s foot (tinea pedis)
- Relieves itching, burning, cracking, and discomfort

Warnings

For external use only.

Avoid contact with eyes.

Do not use

on children under 2 years of age unless directed by a doctor.

If irritation occurs or if there is no improvement within 4 weeks, discontinue use and consult a doctor.

Keep out of reach of children.

If swallowed, get medical help or contact a poison control center right away.

Directions

Wash the affected area and dry thoroughly. Apply a thin layer of the product over affected area twice daily (morning and night) or as directed by a doctor. Supervise children in the use of this product. Pay special attention to spaces between the toes; wear well fitting, ventilated shoes, and change shoes and socks at least once daily. Use daily for 4 weeks. If condition persists longer,
consult a doctor. This product is not effective on the scalp or nails.

Other information

- store at 20o - 25oC (68o - 77oF) [see USP Controlled Room Temperature].

Inactive ingredients

1,2-Hexanediol, Aloe Barbadensis Leaf Juice Powder, Beta-Glucan, Caprylyl Glycol, Fragrance, Glycerin, Potassium Sorbate, Sodium Benzoate, Tapioca Starch, Tricalcium Phosphate, Water, Zea Mays (Corn) Starch

Questions?

call 1-833-279-6522

Principal Display

Desenex®

Antifungal Foot Powder

with 2% Miconazole Nitrate

PRESCRIPTION STRENGTH

Cures Most Athlete's Foot

Triple Action Powder

Relieves Itching, Burning, and Scaling

Attacks and Absorbs Moisture

All Day Odor Control

NET WT. 1.5 oz [43g]

PRODUCT PACKAGED BY WEIGHT NOT VOLUME

©2023 Crown Laboratories, Inc.

Distributed by: Crown Laboratories, Inc . Johnson City, TN 37604

DESENEX is a registered trademark of Crown Laboratories, Inc.

P12319.01